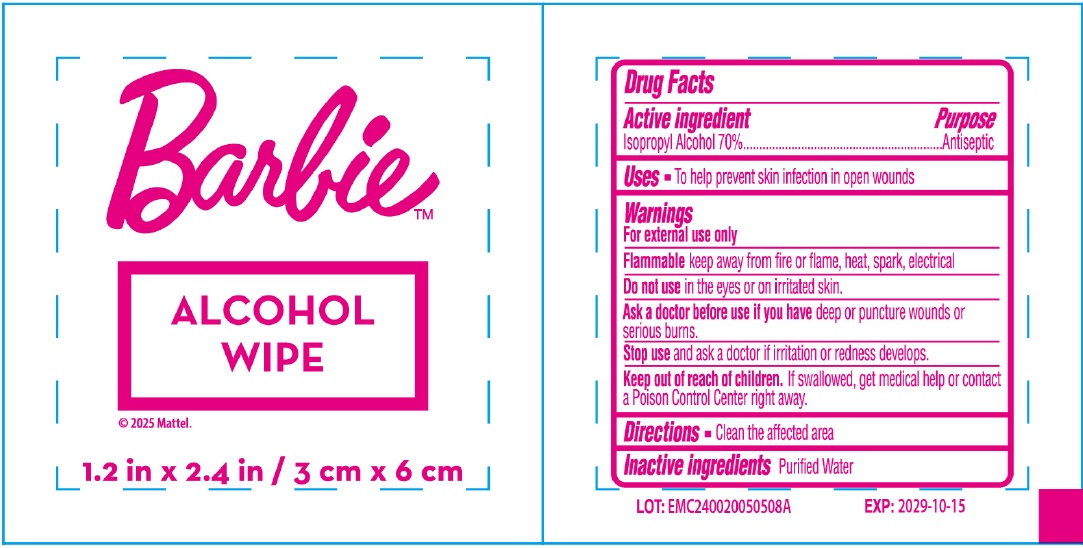 DRUG LABEL: Barbie ALCOHOL WIPE
NDC: 70108-106 | Form: CLOTH
Manufacturer: Ashtel Studios, Inc.
Category: otc | Type: HUMAN OTC DRUG LABEL
Date: 20241108

ACTIVE INGREDIENTS: ISOPROPYL ALCOHOL 70 mL/100 mL
INACTIVE INGREDIENTS: WATER

Barbie™ ALCOHOL WIPE

Active ingredient

Isopropyl Alcohol 70%

Purpose

Antiseptic

Uses

• To help prevent skin infection in open wounds

Warnings

For external use only

Flammable keep away from fire or flame, heat, spark, electrical

Do not use in the eyes or on irritated skin.

Ask a doctor before use if you have deep or puncture wounds or serious burns.

Stop use and ask a doctor if irritation or redness develops.

Keep out of reach of children. If swallowed, get medical help or contact a Poison Control Center right away.

Directions

• Clean the affected area

Inactive ingredients

Purified Water

© 2025 Mattel.